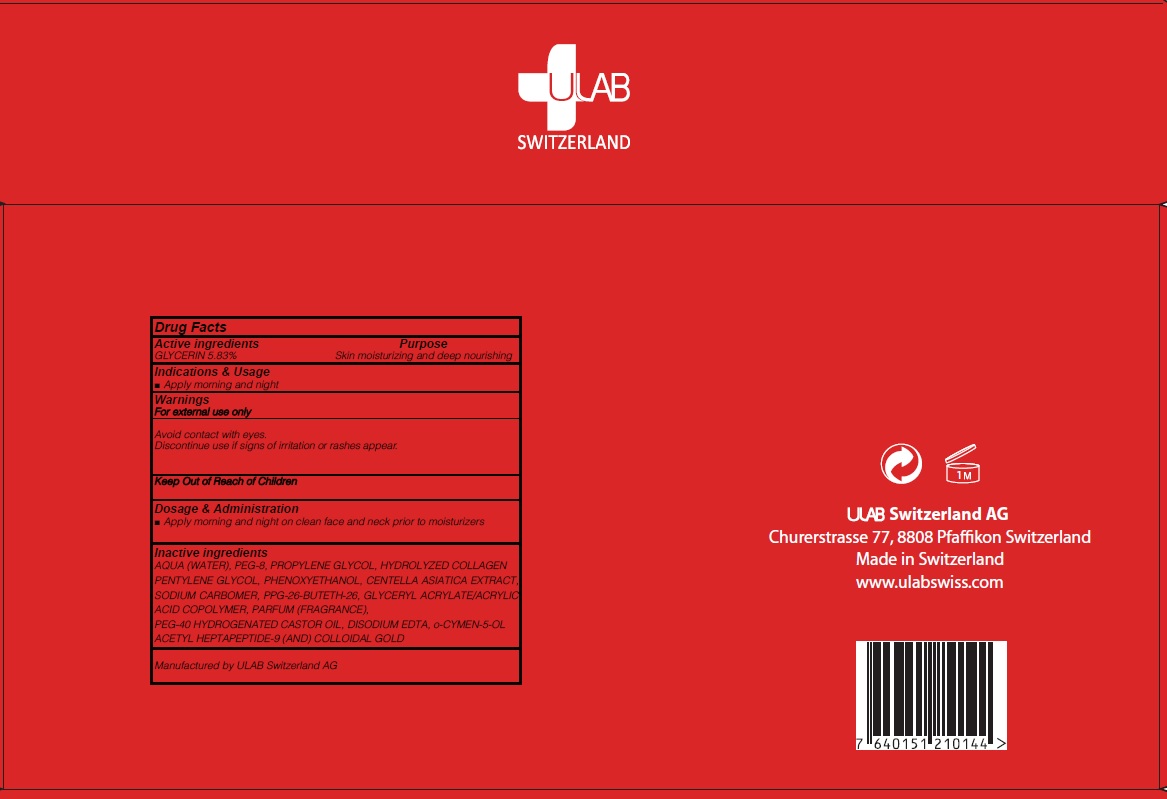 DRUG LABEL: PEPTICOL 5S AMPOULE
NDC: 71276-130 | Form: LIQUID
Manufacturer: ULAB
Category: otc | Type: HUMAN OTC DRUG LABEL
Date: 20170322

ACTIVE INGREDIENTS: GLYCERIN 0.29 g/5 mL
INACTIVE INGREDIENTS: WATER; PROPYLENE GLYCOL

ACTIVE INGREDIENT

Active ingredients: GLYCERIN 5.83%

INACTIVE INGREDIENT

Inactive ingredients: AQUA (WATER), PEG-8, PROPYLENE GLYCOL, HYDROLYZED COLLAGEN PENTYLENE GLYCOL, PHENOXYETHANOL, CENTELLA ASIATICA EXTRACT, SODIUM CARBOMER, PPG-26-BUTETH-26, GLYCERYL ACRYLATE/ACRYLIC ACID COPOLYMER, PARFUM (FRAGRANCE), PEG-40 HYDROGENATED CASTOR OIL, DISODIUM EDTA, o-CYMEN-5-OL ACETYL HEPTAPEPTIDE-9 (AND) COLLOIDAL GOLD

PURPOSE

Purpose: Skin moisturizing and deep nourishing

WARNINGS

Warnings: For external use only Avoid contact with eyes. Discontinue use if signs of irritation or rashes appear.

KEEP OUT OF REACH OF CHILDREN

INDICATIONS & USAGE

Indications & Usage: Apply morning and night

DOSAGE & ADMINISTRATION

Dosage & Administration: Apply morning and night on clean face and neck prior to moisturizers